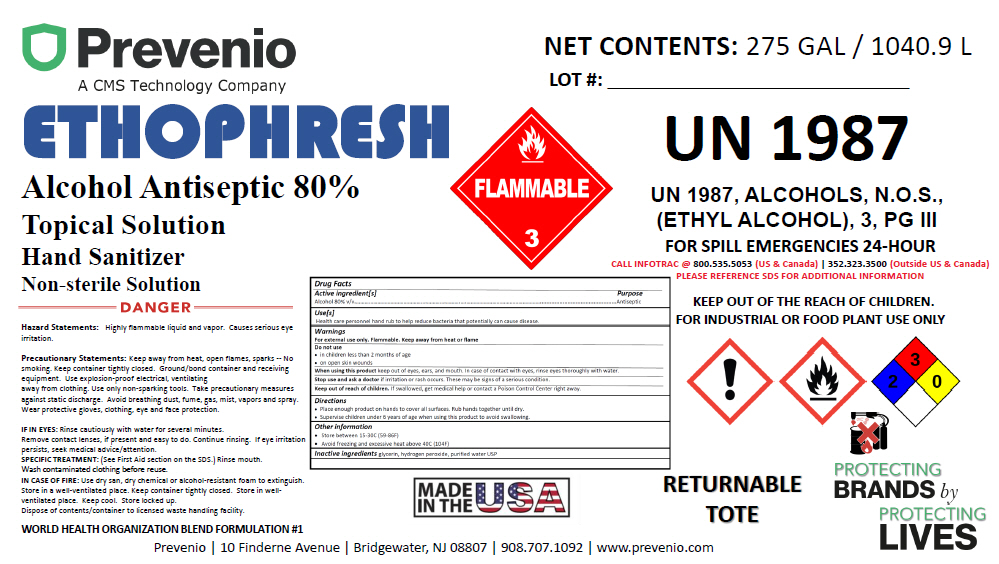 DRUG LABEL: EthopHresh
NDC: 54555-128 | Form: LIQUID
Manufacturer: Brainerd Chemical Company Inc.,
Category: otc | Type: HUMAN OTC DRUG LABEL
Date: 20200430

ACTIVE INGREDIENTS: ALCOHOL 750 mL/1 L
INACTIVE INGREDIENTS: glycerin; hydrogen peroxide; water

EthopHresh

Drug Facts

Active ingredient[s]

Alcohol 80% v/v

Purpose

Antiseptic

Use[s]

Health care personnel hand rub to help reduce bacteria that potentially can cause disease.

Warnings

For external use only. Flammable. Keep away from heat or flame

Do not use

- in children less than 2 months of age
- on open skin wounds

When using this product keep out of eyes, ears, and mouth. In case of contact with eyes, rinse eyes thoroughly with water.

Stop use and ask a doctor if irritation or rash occurs. These may be signs of a serious condition.

Keep out of reach of children. If swallowed, get medical help or contact a Poison Control Center right away.

Directions

- Place enough product on hands to cover all surfaces. Rub hands together until dry.
- Supervise children under 6 years of age when using this product to avoid swallowing.

Other information

- Store between 15-30C (59-86F)
- Avoid freezing and excessive heat above 40C (104F)

Inactive ingredients

glycerin, hydrogen peroxide, purified water USP

PRINCIPAL DISPLAY PANEL - 1040.9 L Tank Label

Prevenio
A CMS Technology Company

ETHOPHRESH
Alcohol Antiseptic 80%
Topical Solution
Hand Sanitizer
Non-sterile Solution

DANGER

Hazard Statements: Highly flammable liquid and vapor. Causes serious eye
irritation.

Precautionary Statements: Keep away from heat, open flames, sparks -- No
smoking. Keep container tightly closed. Ground/bond container and receiving
equipment. Use explosion-proof electrical, ventilating
away from clothing. Use only non-sparking tools. Take precautionary measures
against static discharge. Avoid breathing dust, fume, gas, mist, vapors and spray.
Wear protective gloves, clothing, eye and face protection.

IF IN EYES: Rinse cautiously with water for several minutes.
Remove contact lenses, if present and easy to do. Continue rinsing. If eye irritation
persists, seek medical advice/attention.
SPECIFIC TREATMENT: (See First Aid section on the SDS.) Rinse mouth.
Wash contaminated clothing before reuse.
IN CASE OF FIRE: Use dry san, dry chemical or alcohol-resistant foam to extinguish.
Store in a well-ventilated place. Keep container tightly closed. Store in well-
ventilated place. Keep cool. Store locked up.
Dispose of contents/container to licensed waste handling facility.

WORLD HEALTH ORGANIZATION BLEND FORMULATION #1

FLAMMABLE
3

MADE
IN THE
USA

NET CONTENTS: 275 GAL / 1040.9 L

LOT #: ___________________________

UN 1987

UN 1987, ALCOHOLS, N.O.S.,
(ETHYL ALCOHOL), 3, PG III
FOR SPILL EMERGENCIES 24-HOUR
CALL INFOTRAC @ 800.535.5053 (US & Canada) | 352.323.3500 (Outside US & Canada)
PLEASE REFERENCE SDS FOR ADDITIONAL INFORMATION

KEEP OUT OF THE REACH OF CHILDREN.
FOR INDUSTRIAL OR FOOD PLANT USE ONLY

RETURNABLE
TOTE

PROTECTING
BRANDS by
PROTECTING
LIVES

Prevenio | 10 Finderne Avenue | Bridgewater, NJ 08807 | 908.707.1092 | www.prevenio.com